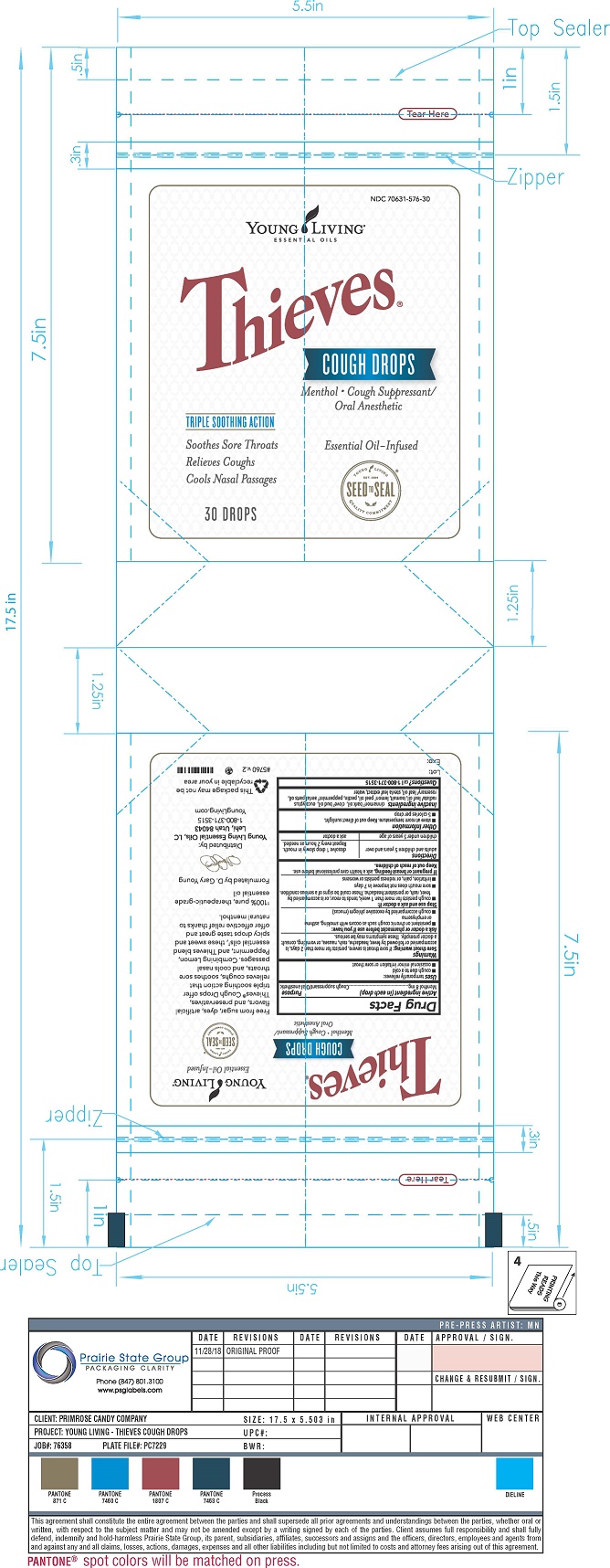 DRUG LABEL: Thieves Cough Drop
NDC: 83240-001 | Form: LOZENGE
Manufacturer: Young Living
Category: otc | Type: HUMAN OTC DRUG LABEL
Date: 20230110

ACTIVE INGREDIENTS: MENTHOL 8 mg/1 1
INACTIVE INGREDIENTS: LEMON OIL; STEVIA LEAF; ISOMALT; PECTIN; PEPPERMINT OIL; ROSEMARY OIL; CINNAMON BARK OIL; CLOVE OIL; EUCALYPTUS RADIATA LEAF OIL

Thieves Menthol Cough Drop

ACTIVE INGREDIENT

Menthol 8mg

PURPOSE

Cough Suppressant / Oral Anesthetic

INDICATIONS AND USAGE

Temporarily relieves:

- cough due to a cold

- occasional minor irritation or sore throat

WARNINGS

Sore Throat Warning: if sore throat is severe, persists for more than 2 days, is accompanied or followed by fever, headache, rash, or vomiting, consult a doctor promptly. These symptoms may be serious.

ASK DOCTOR/PHARMACIST

- persistent or chronic cough such as occurs with smoking, asthma or emphysema

- cough accompanied by excessive phlegm (mucus)

STOP USE

- cough persists for more than 1 seek, tends to recur, or is accompanied by fever, rash, or persistent headache. These could be signs of a serious condition.

- sore mouth does not improve in 7 days

- irritation, pain, or redness persists or worsens

PREGNANCY OR BREAST FEEDING

If pregnant or breast-feeding, ask a health care professional before use.

Keep out of reach of children.

DOSAGE AND ADMINISTRATION

- Adults and children 5 years of age: dissolve 1 drop slowly in mouth. Repeat every 2 hours as needed.

- Children under 5 years of age: ask a doctor

OTHER SAFETY INFORMATION

- store at room temperature. Keep out of direct sunlight.

- 5 calories per drop

INACTIVE INGREDIENT

cinnamon bark oil, clove bud oil, eucalyptus radiata leaf oil, isomalt, lemon peel oil, pectin, peppermint aerial parts oil, rosemary leaf oil, stevia leaf extract, water